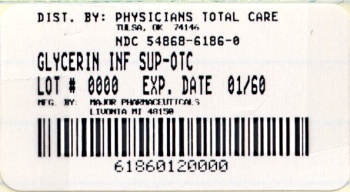 DRUG LABEL: Infant Glycerin Laxative
NDC: 54868-6186 | Form: SUPPOSITORY
Manufacturer: Physicians Total Care, Inc.
Category: otc | Type: HUMAN OTC DRUG LABEL
Date: 20101028

ACTIVE INGREDIENTS: GLYCERIN 1.3 g/1 1
INACTIVE INGREDIENTS: SODIUM STEARATE; WATER

ACTIVE INGREDIENT

Glycerin, USP 80.7%

PURPOSE

Laxative

USE

For relief of occasional constipation

WARNINGS

For rectal use only. May cause rectal discomfort or a burning sensation.

Do not use

- more than one per day
- for a period of longer than one week unless directed by a doctor
- laxative products when abdominal pain, nausea, or vomiting are present unless directed by a doctor
- if seal under product lid is damaged, missing or broken.

Ask a doctor

- before use if you have noticed a sudden change in bowel habits that persists over a period of two weeks
- if you are pregnant or nursing a baby

Stop use and ask a doctor

- if you have rectal bleeding or fail to have a bowel movement after using a laxative. This may indicate a serious condition.

Keep out of reach of children

- If swallowed, get medical help or contact a Poison Control Center right away.

ASK DOCTOR/PHARMACIST

Enter section text here

WHEN USING

Enter section text here

PREGNANCY OR BREAST FEEDING

Enter section text here

DIRECTIONS

- Children 2 - 6 years of age: carefully insert one suppository well into the rectum
- Do not use more than once per day
- Generally produces a bowel movement in 15 minutes to 1 hour
- Children under 2 years of age: ask a doctor.

OTHER INFORMATION

- Store container tightly closed
- Store at room temperature: 15°- 30° C (59° - 86° F). Do not exceed 30° C (86° F).

INACTIVE INGREDIENTS

sodium stearate, purified water

QUESTIONS

Adverse Drug Event Call: (800) 616-2471

PRINCIPAL DISPLAY PANEL

NDC 54868-6186-0
Infant
GLYCERIN
SUPPOSITORIES

Rectal evacuant
For relief of
temporary constipation
12 Infant Suppositories

Compare to Fleet® Glycerin Suppositories*
*This product is not manufactured or distributed by C.B.Fleet co., owner of
the registered trademark Fleet®.

Distributed by:
Major Pharmaceuticals
31778 Enterprise Drive
Livonia, MI 48150 USA

Reorder No. 233874
M-54 Rev 6/08

DO NOT USE IF PRINTED
INNER SEAL IS BROKEN
OR MISSING

Relabeling of "Additional Barcode Label" by:
Physicians Total Care, Inc.
Tulsa, OK 74146